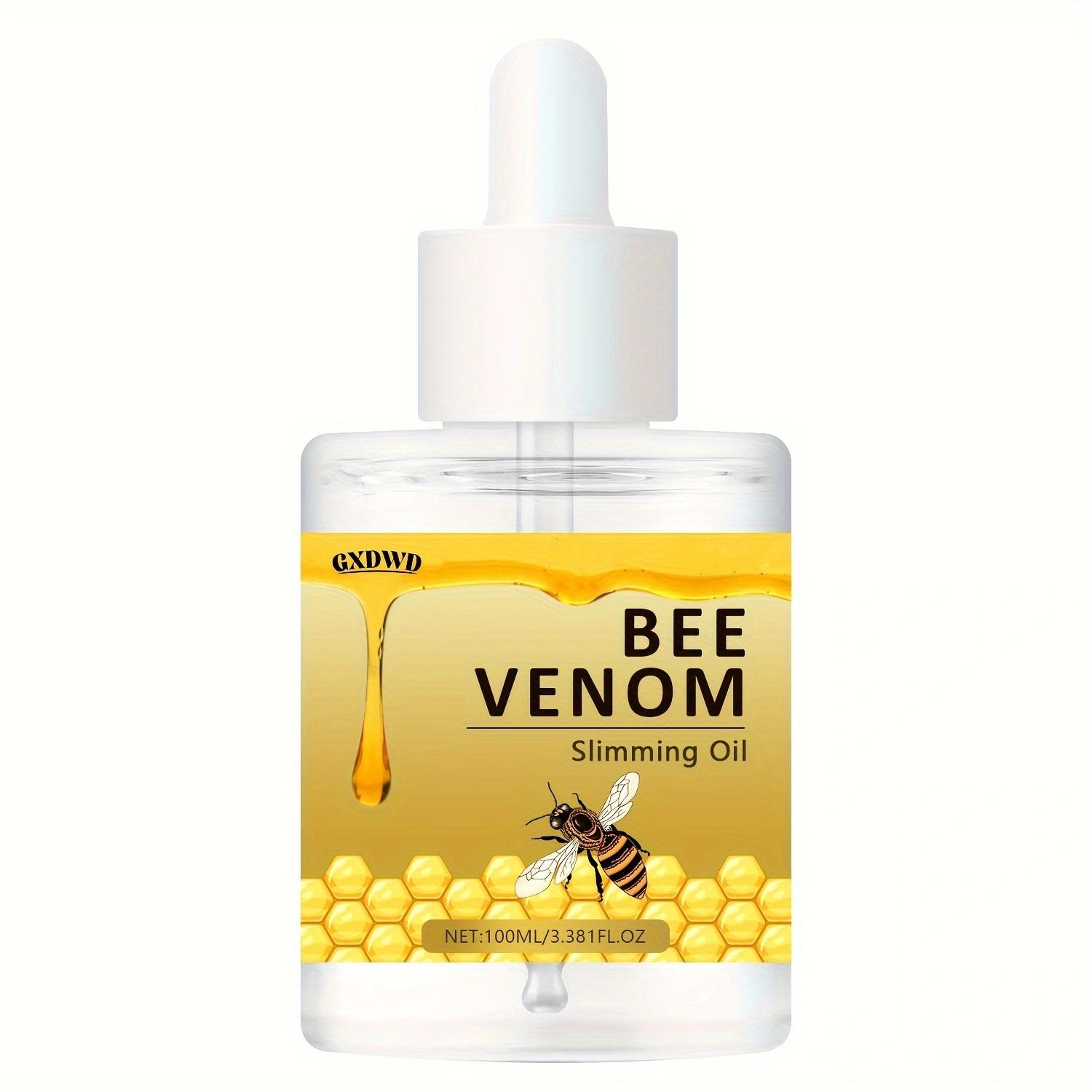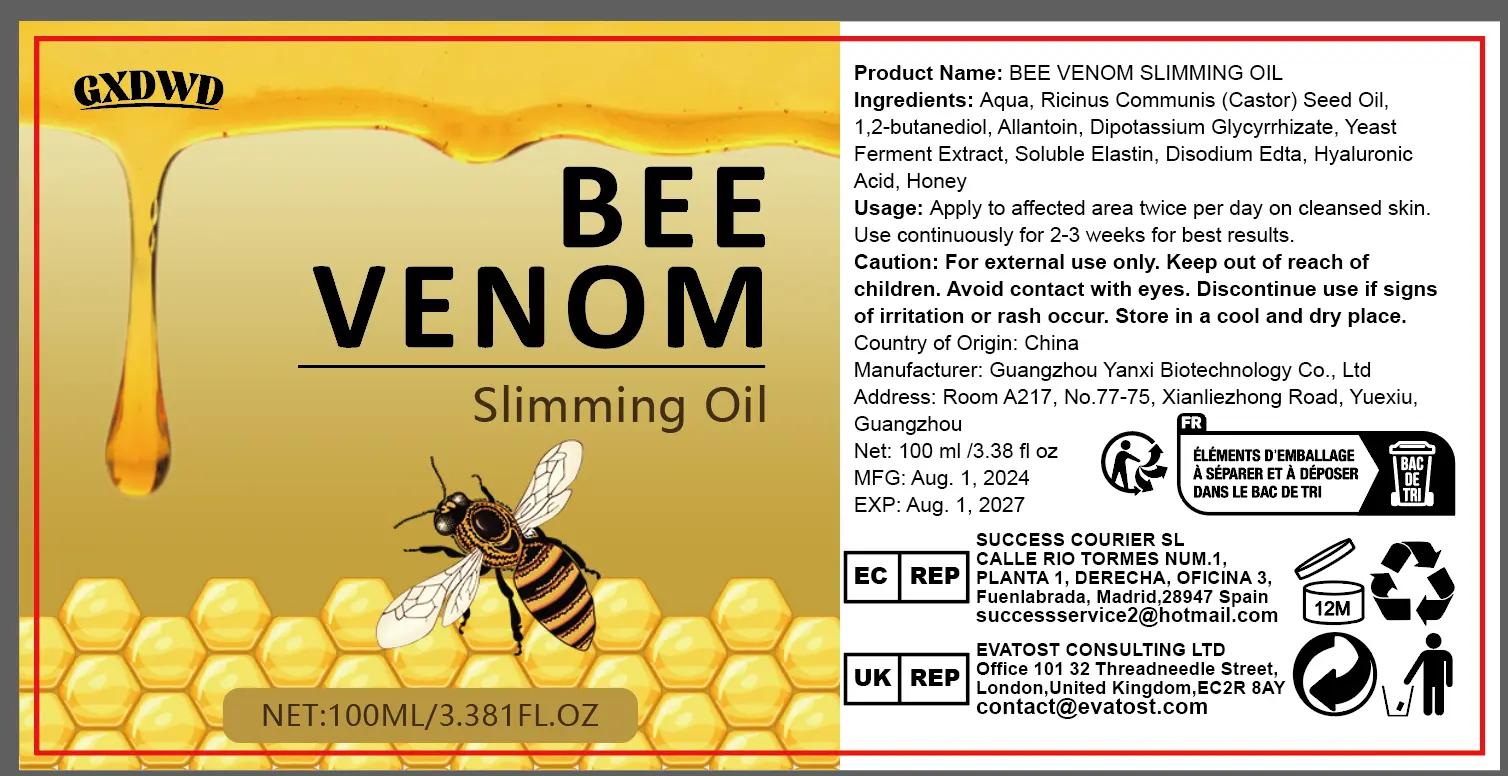 DRUG LABEL: BEE VENOM Slimming Oil
NDC: 84025-246 | Form: OIL
Manufacturer: Guangzhou Yanxi Biotechnology Co., Ltd
Category: otc | Type: HUMAN OTC DRUG LABEL
Date: 20241104

ACTIVE INGREDIENTS: RICINUS COMMUNIS (CASTOR) SEED OIL 5 mg/100 mL; 1,2-BUTANEDIOL 3 mg/100 mL
INACTIVE INGREDIENTS: WATER

DOSAGE AND ADMINISTRATION

Apply to affected area twice per day on cleansed skin. Use continuously for 2-3 weeks for best results.

WARNINGS

Keep out of children

INACTIVE INGREDIENT

Aqua

INDICATIONS AND USAGE

for face care

keep out of children

PURPOSE

helps to nourish and moisturize the skin. Regular use can make the skin more moisturized and radiant